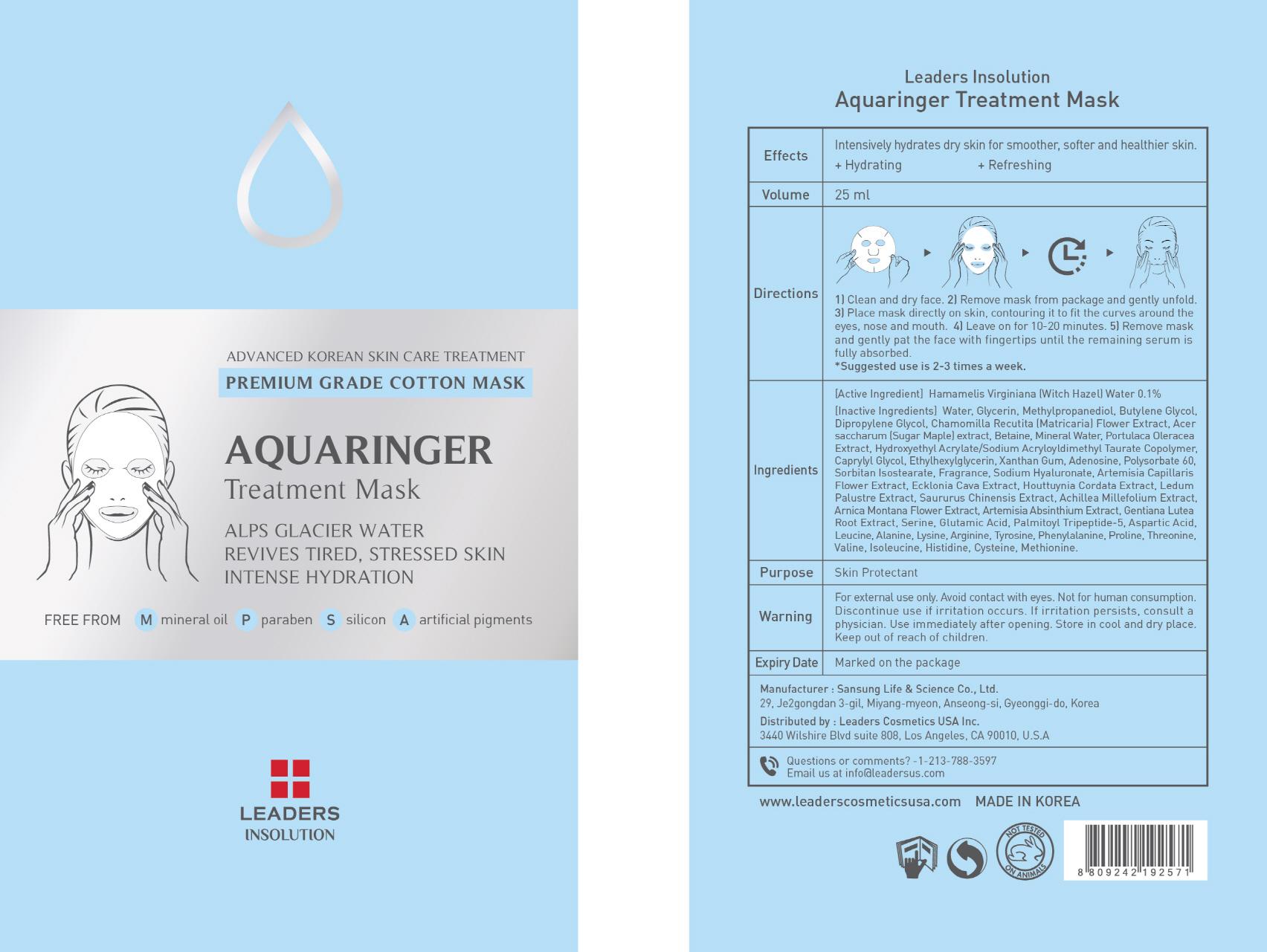 DRUG LABEL: AQUARINGER TREATMENT MASK
NDC: 69424-040 | Form: PATCH
Manufacturer: SANSUNG LIFE & SCIENCE CO., LTD.
Category: otc | Type: HUMAN OTC DRUG LABEL
Date: 20151204

ACTIVE INGREDIENTS: Witch Hazel 25 mg/25 mL
INACTIVE INGREDIENTS: Water; Glycerin

ACTIVE INGREDIENT

Active Ingredient: Hamamelis Virginiana (Witch Hazel) Water 0.1%

INACTIVE INGREDIENT

Inactive Ingredients: Water, Glycerin, Methylpropanediol, Butylene Glycol, Dipropylene Glycol, Chamomilla Recutita (Matricaria) Flower Extract, Acer saccharum (Sugar Maple) extract, Betaine, Mineral Water, Portulaca Oleracea Extract, Hydroxyethyl Acrylate/Sodium Acryloyldimethyl Taurate Copolymer, Caprylyl Glycol, Ethylhexylglycerin, Xanthan Gum, Adenosine, Polysorbate 60, Sorbitan Isostearate, Fragrance, Sodium Hyaluronate, Artemisia Capillaris Flower Extract, Ecklonia Cava Extract, Houttuynia Cordata Extract, Ledum Palustre Extract, Saururus Chinensis Extract, Achillea Millefolium Extract, Arnica Montana Flower Extract, Artemisia Absinthium Extract, Gentiana Lutea Root Extract, Serine, Glutamic Acid, Palmitoyl Tripeptide-5, Aspartic Acid, Leucine, Alanine, Lysine, Arginine, Tyrosine, Phenylalanine, Proline, Threonine, Valine, Isoleucine, Histidine, Cysteine, Methionine.

PURPOSE

Purpose: Skin Protectant

WARNINGS

Warning: For external use only. Avoid contact with eyes. Not for human consumption. Discontinue use if irritation occurs. If irritation persists, consult a physician. Use immediately after opening. Store in cool and dry place. Keep out of reach of children.

KEEP OUT OF REACH OF CHILDREN

Directions

Directions 1) Clean and dry face. 2) Remove mask from package and gently unfold. 3) Place mask directly on skin, contouring it to fit the curves around the eyes, nose and mouth. 4) Leave on for 10-20 minutes. 5) Remove mask and gently pat the face with fingertips until the remaining serum is fully absorbed. *Suggested use is 2-3 times a week.

Directions

Directions 1) Clean and dry face. 2) Remove mask from package and gently unfold. 3) Place mask directly on skin, contouring it to fit the curves around the eyes, nose and mouth. 4) Leave on for 10-20 minutes. 5) Remove mask and gently pat the face with fingertips until the remaining serum is fully absorbed. *Suggested use is 2-3 times a week.